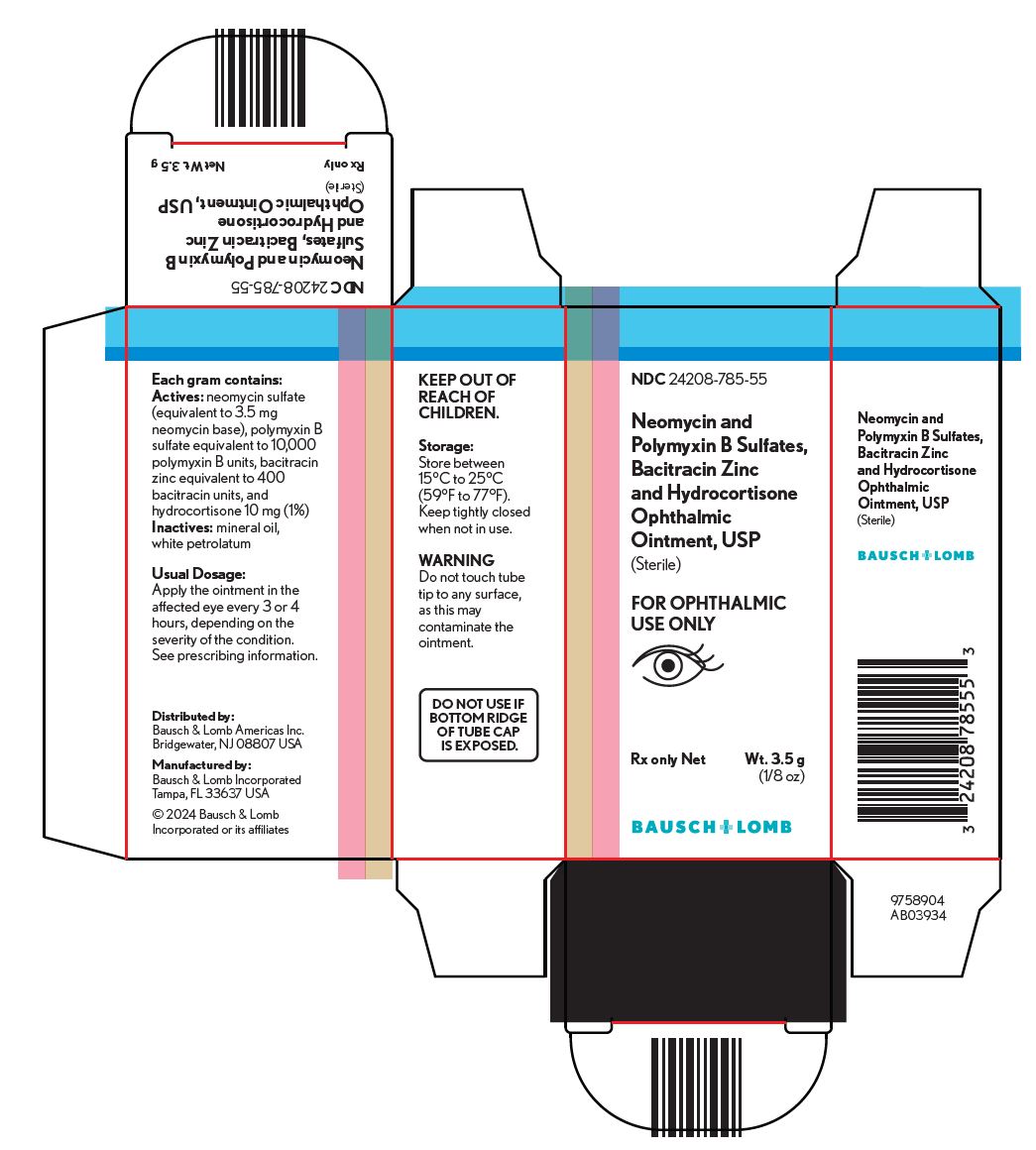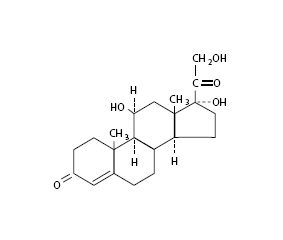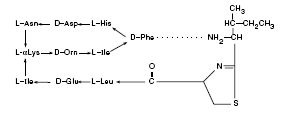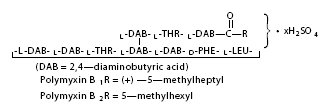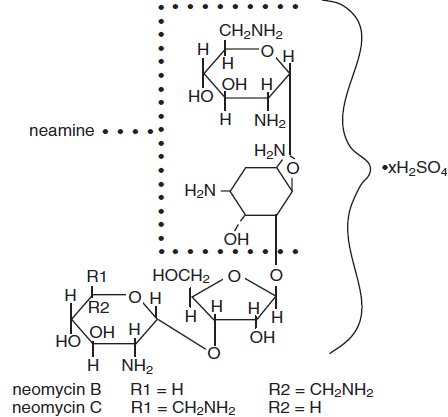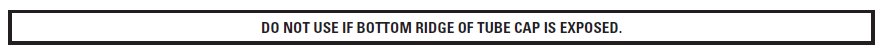 DRUG LABEL: Neomycin and Polymyxin B Sulfates, Bacitracin Zinc and Hydrocortisone
NDC: 24208-785 | Form: OINTMENT
Manufacturer: Bausch & Lomb Incorporated
Category: prescription | Type: HUMAN PRESCRIPTION DRUG LABEL
Date: 20250102

ACTIVE INGREDIENTS: NEOMYCIN SULFATE 3.5 mg/1 g; POLYMYXIN B SULFATE 10000 [USP'U]/1 g; BACITRACIN ZINC 400 [USP'U]/1 g; HYDROCORTISONE 10 mg/1 g
INACTIVE INGREDIENTS: MINERAL OIL; PETROLATUM

Neomycin and Polymyxin B Sulfates,
Bacitracin Zinc and Hydrocortisone
Ophthalmic Ointment, USP
(Sterile)
Rx only

DESCRIPTION

Neomycin and polymyxin B sulfates, bacitracin zinc and hydrocortisone ophthalmic ointment, USP is a sterile antimicrobial and anti-inflammatory ointment for ophthalmic use.

Each gram contains:

Actives:neomycin sulfate equivalent to 3.5 mg neomycin base, polymyxin B sulfate equivalent to 10,000 polymyxin B units, bacitracin zinc equivalent to 400 bacitracin units, hydrocortisone 10 mg (1%); Inactives:mineral oil, white petrolatum.

Neomycin sulfate is the sulfate salt of neomycin B and C, which are produced by the growth of Streptomyces fradiae Waksman (Fam. Streptomycetaceae). It has a potency equivalent of not less than 600 mcg of neomycin standard per mg, calculated on an anhydrous basis.

The structural formulae are:

Polymyxin B sulfate is the sulfate salt of polymyxin B1 and B2, which are produced by the growth of Bacillus polymyxa (Prazmowski) Migula (Fam. Bacillaceae). It has a potency of not less than 6,000 polymyxin B units per mg, calculated on an anhydrous basis.

The structural formulae are:

Bacitracin zinc is the zinc salt of bacitracin, a mixture of related cyclic polypeptides (mainly bacitracin A) produced by the growth of an organism of the licheniformis group of Bacillus subtilis var Tracy. It has a potency of not less than 40 bacitracin units per mg.

The structural formula is:

Hydrocortisone, 11β, 17, 21-trihydroxypregn-4-ene-3, 20-dione, is an anti-inflammatory hormone.

Its structural formula is:

CLINICAL PHARMACOLOGY

Corticosteroids suppress the inflammatory response to a variety of agents and they probably delay or slow healing. Since corticosteroids may inhibit the body’s defense mechanism against infection, concomitant antimicrobial drugs may be used when this inhibition is considered to be clinically significant in a particular case.

When a decision to administer both a corticosteroid and antimicrobials is made, the administration of such drugs in combination has the advantage of greater patient compliance and convenience, with the added assurance that the appropriate dosage of all drugs is administered. When each type of drug is in the same formulation, compatibility of ingredients is assured and the correct volume of drug is delivered and retained.

The relative potency of corticosteroids depends on the molecular structure, concentration, and release from the vehicle.

Microbiology

The anti-infective components in neomycin and polymyxin B sulfates, bacitracin zinc and hydrocortisone ophthalmic ointment are included to provide action against specific organisms susceptible to it. Neomycin sulfate and polymyxin B sulfate are active in vitro against susceptible strains of the following microorganisms: Staphylococcus aureus, streptococci including Streptococcus pneumoniae, Escherichia coli, Haemophilus influenzae, Klebsiella/Enterobacter species, Neisseria species, and Pseudomonas aeruginosa. This product does not provide adequate coverage against Serratia marcescens(see INDICATIONS AND USAGE).

INDICATIONS AND USAGE

Neomycin and polymyxin B sulfates, bacitracin zinc and hydrocortisone ophthalmic ointment is indicated for steroid-responsive inflammatory ocular conditions for which a corticosteroid is indicated and where bacterial infection or a risk of bacterial infection exists.

Ocular corticosteroids are indicated in inflammatory conditions of the palpebral and bulbar conjunctiva, cornea, and anterior segment of the globe where the inherent risk of corticosteroid use in certain infective conjunctivitides is accepted to obtain a diminution in edema and inflammation. They are also indicated in chronic anterior uveitis and corneal injury from chemical, radiation, or thermal burns, or penetration of foreign bodies.

The use of a combination drug with an anti-infective component is indicated where the risk of infection is high or where there is an expectation that potentially dangerous numbers of bacteria will be present in the eye (see CLINICAL PHARMACOLOGY, Microbiology).

The particular anti-infective drugs in this product are active against the following common bacterial eye pathogens: Staphylococcus aureus, streptococci, including Streptococcus pneumoniae, Escherichia coli, Haemophilus influenzae, Klebsiella/Enterobacter species, Neisseria species, and Pseudomonas aeruginosa. The product does not provide adequate coverage against Serratia marcescens.

CONTRAINDICATIONS

Neomycin and polymyxin B sulfates, bacitracin zinc and hydrocortisone ophthalmic ointment is contraindicated in most viral diseases of the cornea and conjunctiva including: epithelial herpes simplex keratitis (dendritic keratitis), vaccinia and varicella, and also in mycobacterial infection of the eye and fungal diseases of ocular structures.

Neomycin and polymyxin B sulfates, bacitracin zinc and hydrocortisone ophthalmic ointment is also contraindicated in individuals who have shown hypersensitivity to any of its components. Hypersensitivity to the antibiotic component occurs at a higher rate than for other components.

WARNINGS

NOT FOR INJECTION INTO THE EYE
Neomycin and polymyxin B sulfates, bacitracin zinc and hydrocortisone ophthalmic ointment should never be directly introduced into the anterior chamber of the eye. Ophthalmic ointments may retard corneal wound healing. Prolonged use of corticosteroids may result in ocular hypertension and/or glaucoma, with damage to the optic nerve, defects in visual acuity and fields of vision, and in posterior subcapsular cataract formation.

Prolonged use may suppress the host immune response and thus increase the hazard of secondary ocular infections. Various ocular diseases and long-term use of topical corticosteroids have been known to cause corneal and scleral thinning. Use of topical corticosteroids in the presence of thin corneal or scleral tissue may lead to perforation.

Acute purulent infections of the eye may be masked or enhanced by the presence of corticosteroid medication.

If these products are used for 10 days or longer, intraocular pressure should be routinely monitored even though it may be difficult in uncooperative patients. Corticosteroids should be used with caution in the presence of glaucoma. Intraocular pressure should be checked frequently.

The use of corticosteroids after cataract surgery may delay healing and increase the incidence of filtering blebs.

Use of ocular corticosteroids may prolong the course and may exacerbate the severity of many viral infections of the eye (including herpes simplex). Employment of corticosteroid medication in the treatment of herpes simplex requires great caution; frequent slit lamp microscopy is recommended.

Topical antibiotics, particularly neomycin sulfate, may cause cutaneous sensitization. A precise incidence of hypersensitivity reactions (primarily skin rash) due to topical antibiotics is not known. The manifestations of sensitization to topical antibiotics are usually itching, reddening, and edema of the conjunctiva and eyelid. A sensitization reaction may manifest simply as a failure to heal. During long-term use of topical antibiotic products, periodic examination for such signs is advisable, and the patient should be told to discontinue the product if they are observed. Symptoms usually subside quickly on withdrawing the medication. Applications of products containing these ingredients should be avoided for the patient thereafter (see PRECAUTIONS, General).

PRECAUTIONS

General

The initial prescription and renewal of the medication order beyond 8 grams should be made by a physician only after examination of the patient with the aid of magnification, such as slit lamp biomicroscopy and, where appropriate, fluorescein staining. If signs and symptoms fail to improve after two days, the patient should be re-evaluated.

As fungal infections of the cornea are particularly prone to develop coincidentally with long-term corticosteroid applications, fungal invasion should be suspected in any persistent corneal ulceration where a corticosteroid has been used or is in use. Fungal cultures should be taken when appropriate.

If this product is used for 10 days or longer, intraocular pressure should be monitored (see WARNINGS).

There have been reports of bacterial keratitis associated with the use of topical ophthalmic products in multiple-dose containers which have been inadvertently contaminated by patients, most of whom had a concurrent corneal disease or a disruption of the ocular epithelial surface (see PRECAUTIONS, Information for Patients).

Allergic cross-reactions may occur which could prevent the use of any or all of the following antibiotics for the treatment of future infections: kanamycin, paromomycin, streptomycin, and possibly gentamicin.

Information for Patients

If inflammation or pain persists longer than 48 hours or becomes aggravated, the patient should be advised to discontinue use of the medication and consult a physician.

This product is sterile when packaged. To prevent contamination, care should be taken to avoid touching the tip of the tube to eyelids or to any other surface. The use of this tube by more than one person may spread infection. Store at 15°C to 25°C (59°F to 77°F). Keep out of the reach of children.

Carcinogenesis, Mutagenesis, Impairment of Fertility

Long-term studies in animals to evaluate carcinogenic or mutagenic potential have not been conducted with polymyxin B sulfate or bacitracin. Treatment of cultured human lymphocytes in vitro with neomycin increased the frequency of chromosome aberrations at the highest concentration (80 mcg/mL) tested; however, the effects of neomycin on carcinogenesis and mutagenesis in humans are unknown.

Long-term studies in animals (rats, rabbits, mice) showed no evidence of carcinogenicity or mutagenicity attributable to oral administration of corticosteroids. Long-term animal studies have not been performed to evaluate the carcinogenic potential of topical corticosteroids. Studies to determine mutagenicity with hydrocortisone have revealed negative results.

Polymyxin B has been reported to impair the motility of equine sperm, but its effects on male or female fertility are unknown. No adverse effects on male or female fertility, litter size or survival were observed in rabbits given bacitracin zinc 100 gm/ton of diet. Long-term animal studies have not been performed to evaluate the effect on fertility of topical corticosteroids.

Pregnancy: Teratogenic Effects

Corticosteroids have been found to be teratogenic in rabbits when applied topically at concentrations of 0.5% on days 6 to 18 of gestation and in mice when applied topically at a concentration of 15% on days 10 to 13 of gestation. There are no adequate and well-controlled studies in pregnant women. Neomycin and polymyxin B sulfates, bacitracin zinc and hydrocortisone ophthalmic ointment should be used during pregnancy only if the potential benefit justifies the potential risk to the fetus.

Nursing Mothers

It is not known whether topical administration of corticosteroids could result in sufficient systemic absorption to produce detectable quantities in human milk. Systemically administered corticosteroids appear in human milk and could suppress growth, interfere with endogenous corticosteroid production, or cause other untoward effects. Because of the potential for serious adverse reactions in nursing infants from neomycin and polymyxin B sulfates, bacitracin zinc and hydrocortisone ophthalmic ointment, a decision should be made whether to discontinue nursing or to discontinue the drug, taking into account the importance of the drug to the mother.

Pediatric Use

Safety and effectiveness in pediatric patients have not been established.

Geriatric Use

No overall differences in safety or effectiveness have been observed in between elderly and younger patients.

ADVERSE REACTIONS

Adverse reactions have occurred with corticosteroid/anti-infective combination drugs which can be attributed to the corticosteroid component, the anti-infective component, or the combination. The exact incidence is not known.

Reactions occurring most often from the presence of the anti-infective ingredient are allergic sensitization reactions including itching, swelling, and conjunctival erythema (see WARNINGS). More serious hypersensitivity reactions, including anaphylaxis, have been reported rarely.

The reactions due to the corticosteroid component in decreasing order of frequency are: elevation of intraocular pressure (IOP) with possible development of glaucoma, and infrequent optic nerve damage; posterior subcapsular cataract formation; and delayed wound healing.

Secondary Infection

The development of secondary ocular infection has occurred after use of combinations containing corticosteroids and antimicrobials. Fungal and viral infections of the cornea are particularly prone to develop coincidentally with long-term applications of a corticosteroid. The possibility of fungal invasion must be considered in any persistent corneal ulceration where corticosteroid treatment has been used (see WARNINGS).

Local irritation on instillation has also been reported.

If signs and symptoms fail to improve after two days, the patient should be re-evaluated (see PRECAUTIONS).

To report SUSPECTED ADVERSE REACTIONS, contact Bausch & Lomb Incorporated at 1-800-553-5340 or FDA at 1-800-FDA-1088 or www.fda.gov/medwatch.

DOSAGE AND ADMINISTRATION

Apply the ointment in the affected eye every 3 or 4 hours, depending on the severity of the condition.

Not more than 8 grams should be prescribed initially and the prescription should not be refilled without further evaluation as outlined in PRECAUTIONSabove.

HOW SUPPLIED

Neomycin and polymyxin B sulfates, bacitracin zinc and hydrocortisone ophthalmic ointment, USP is supplied in a tube with ophthalmic tip applicator in the following size:

NDC 24208-785-55 - 3.5 g tube

FOR OPHTHALMIC USE ONLY

Storage

Store at 15°C to 25°C (59°F to 77°F). Keep tightly closed when not in use.

KEEP OUT OF REACH OF CHILDREN.

Distributed by:
Bausch & Lomb Americas Inc.
Bridgewater, NJ 08807 USA

Manufactured by:
Bausch & Lomb Incorporated
Tampa, FL 33637 USA

© 2023 Bausch & Lomb Incorporated or its affiliates

Rev. 01/2023

9113804 (Folded)

9113904 (Flat)

PACKAGE/LABEL PRINCIPAL DISPLAY PANEL

NDC24208-785-55

Neomycin and
Polymyxin B Sulfates,
Bacitracin Zinc
and Hydrocortisone
Ophthalmic
Ointment, USP
(Sterile)

FOR OPHTHALMIC
USE ONLY

{eye image}

Rx only Net Wt. 3.5 g

(1/8 oz)

BAUSCH + LOMB

9758904
AB03934